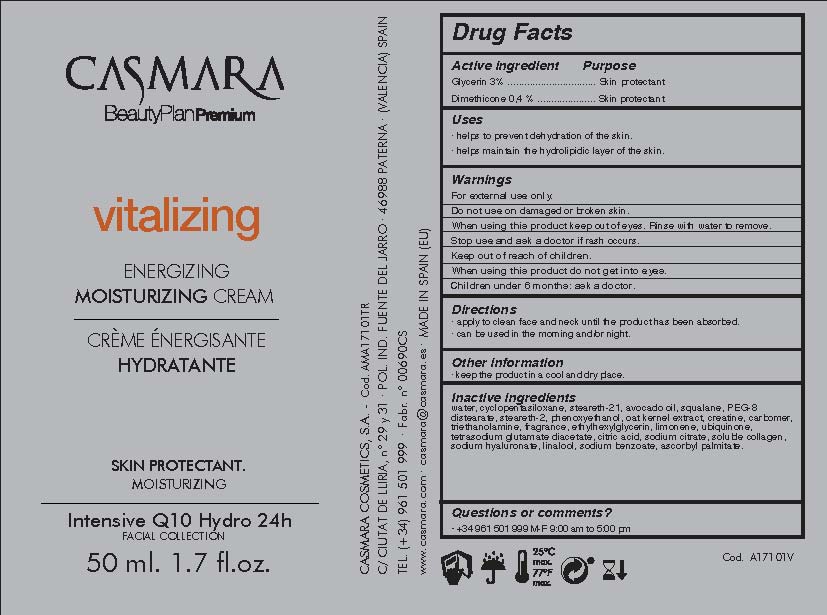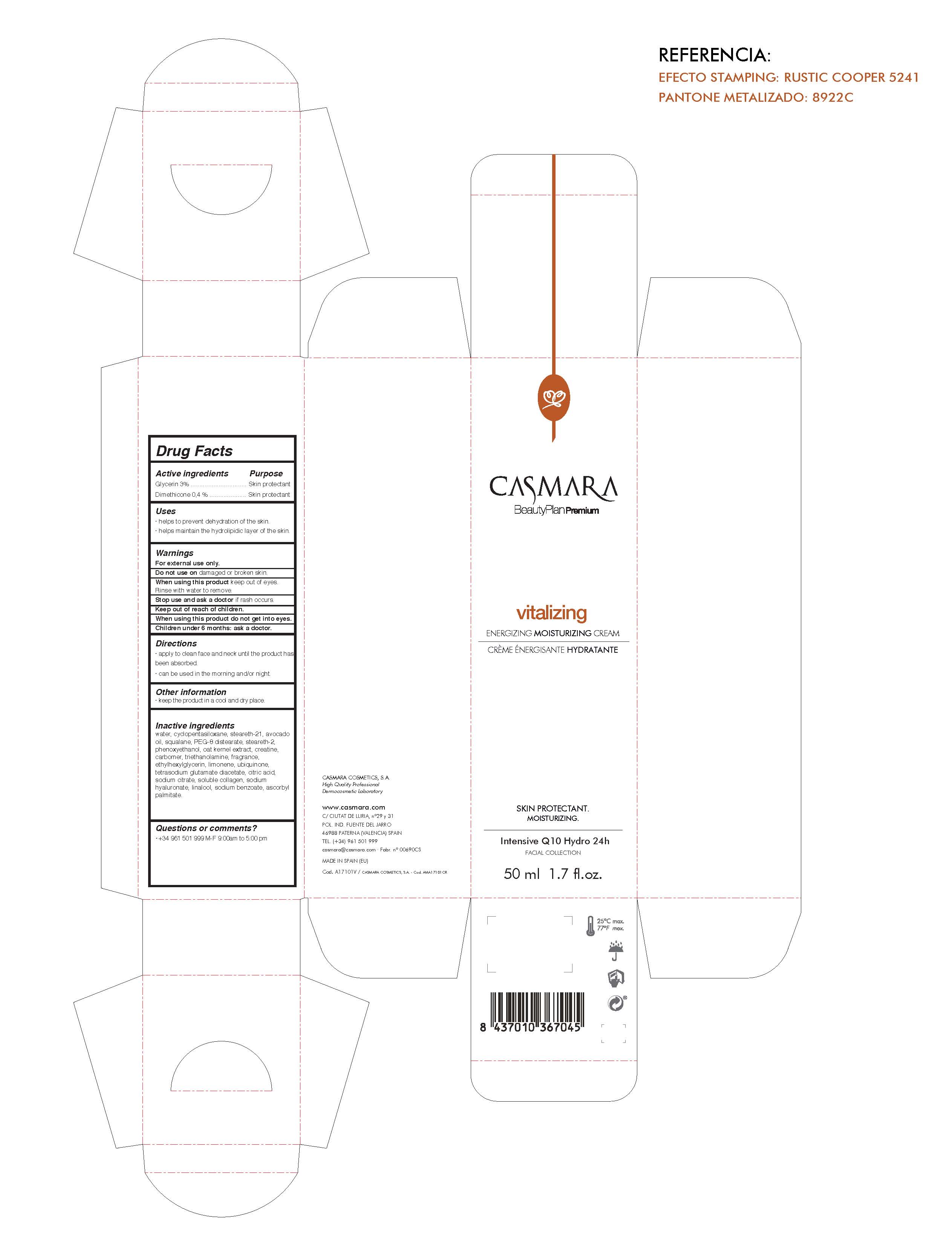 DRUG LABEL: Vitalizing Energizing Moisturizing Cream
NDC: 20151-089 | Form: CREAM
Manufacturer: Casmara Cosmetics, SA
Category: otc | Type: HUMAN OTC DRUG LABEL
Date: 20170223

ACTIVE INGREDIENTS: GLYCERIN 3 mg/1 mL; DIMETHICONE 0.4 mg/1 mL
INACTIVE INGREDIENTS: CYCLOMETHICONE 5 3 mg/1 mL; CARBOXYPOLYMETHYLENE 0.5 mg/1 mL; PEG-8 DISTEARATE 2 mg/1 mL; STEARETH-2 2 mg/1 mL; ETHYLHEXYLGLYCERIN 0.1 mg/1 mL; WATER 78.27 mg/1 mL; PERFLUNAFENE 0.3 mg/1 mL; PHENOXYETHANOL 0.9 mg/1 mL; LIMONENE, (+)- 0.104 mg/1 mL; TETRASODIUM GLUTAMATE DIACETATE 0.094 mg/1 mL; UBIQUINOL 0.1 mg/1 mL; OAT KERNEL OIL 0.52 mg/1 mL; LINALOOL, (+)- 0.019 mg/1 mL; CITRIC ACID MONOHYDRATE 0.045 mg/1 mL; ASCORBYL PALMITATE 0.001 mg/1 mL; MARINE COLLAGEN, SOLUBLE 0.025 mg/1 mL; HYALURONATE SODIUM 0.02 mg/1 mL; SODIUM BENZOATE 0.0125 mg/1 mL; CREATINE 0.5 meq/1 mL; AVOCADO OIL 2.6 mg/1 mL; SODIUM CITRATE 0.027 mg/1 mL; SQUALANE 2 mg/1 mL; TROLAMINE 0.4 mg/1 mL; STEARETH-21 3 meq/1 mL

Vitalizing Energizing Moisturizing Cream

Warnings

For external use only.

Do not use on damaged or broken skin.

When using this product keep our of the eyes. Rinse with water to remove.

Stop use and ask a doctor if rash occurs.

Keep out of reach of children.

Whhen using this product do not get into eyes.

Children under 6 months: as a doctor.

WARNINGS

Stop use and ask a doctor if rash occurs

Children under 6 months: ask a doctor

Warnings

Keep out of reach of children

Questions or comments?

+ 34 961 501 999 M-F 9:00 am to 5:00 pm

Other Information

. keep the product in a cool and dry place

Directions

. apply every day gently onto clean face and neck until the product has been absorbed

. can be used in the morning and/or night

DOSAGE AND ADMINISTRATION

. apply every day gently onto clean dace and neck until the product has been absorbed

. can be used in the morning and/or night

Uses

. provides an intensive dose of hydration and energy

Inactive Ingredients

water, cyclopentasiloxane, steareth-21, avocado oil, squalane, PEG-8 distearate, steareth-2, phenoxyethanol, avena sativa (oak) kernel extract, creatine, carbomer, triethanolamine, parfum, ethylhexylglycerin, limonene, ubiquinone, tetrasodium glutamate diacetate, citric acid, sodium citrate, soluble collage, sodium hyaluronate, linalool, sodium benzoate, ascorbyl palmitate

Uses

. provides an intense dose of hydration and energy

ACTIVE INGREDIENTS PURPOSE

Glycerin 5%.................... Skin Protectant

Dimethicone 0.40%.........Skin Protectant

See below image

Vitalizing Energizing Moisturizing Cream

Skin Protectant

Nourishing

Intensive Q 10 Hydro 24 h

Package Label

Please see image below. Package Label